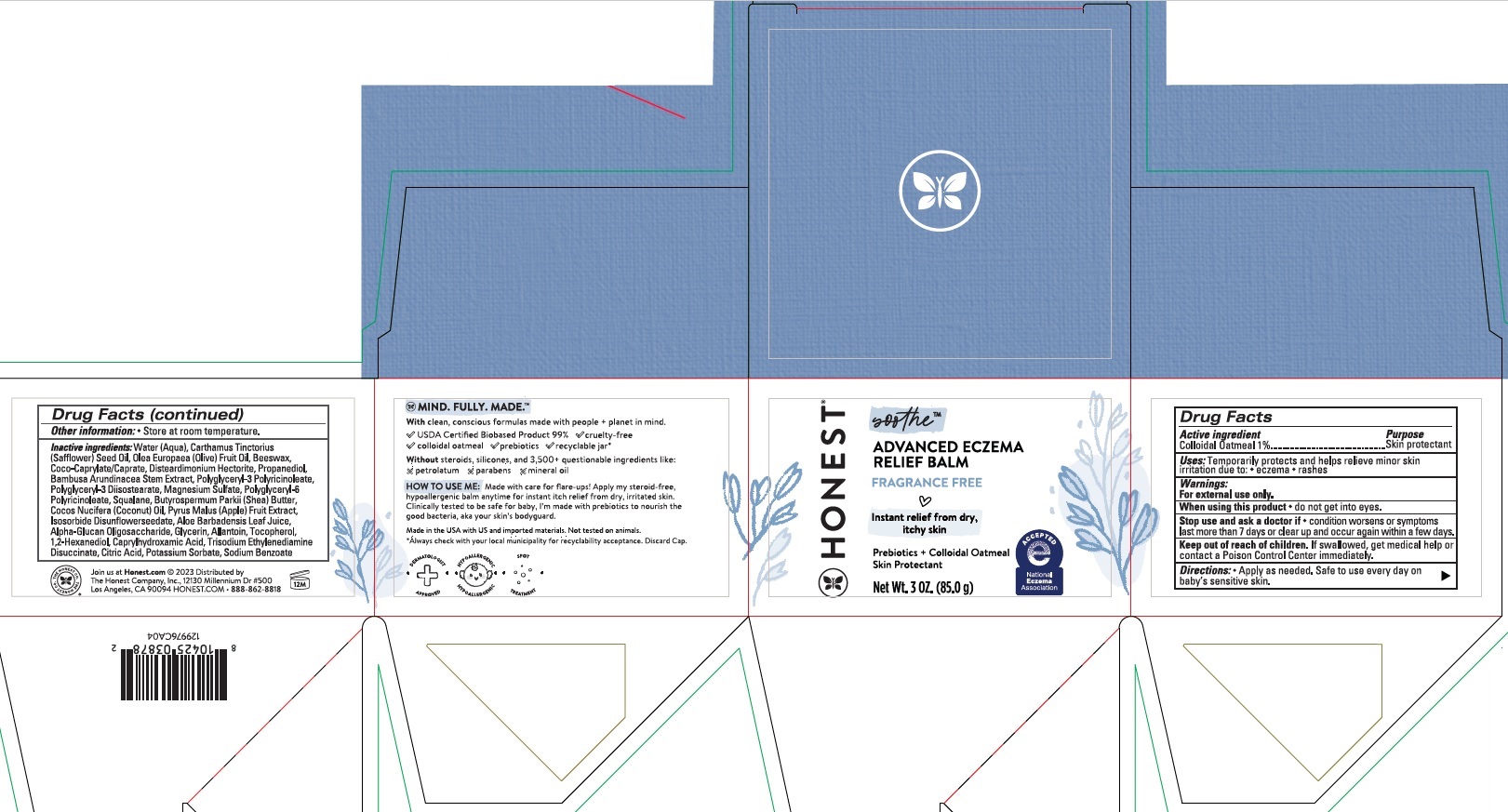 DRUG LABEL: Honest Eczema Balm
NDC: 69366-503 | Form: OINTMENT
Manufacturer: The Honest Company, Inc.
Category: otc | Type: HUMAN OTC DRUG LABEL
Date: 20240514

ACTIVE INGREDIENTS: OATMEAL 1 g/100 g
INACTIVE INGREDIENTS: WATER; SAFFLOWER OIL; OLIVE OIL; YELLOW WAX; COCO-CAPRYLATE/CAPRATE; DISTEARDIMONIUM HECTORITE; PROPANEDIOL; BAMBUSA BAMBOS STEM; POLYGLYCERYL-3 RICINOLEATE; MAGNESIUM SULFATE, UNSPECIFIED FORM; SHEA BUTTER; COCONUT OIL; APPLE; ALOE VERA LEAF; .ALPHA.-GLUCAN OLIGOSACCHARIDE; GLYCERIN; SQUALANE; ALLANTOIN; TOCOPHEROL; 1,2-HEXANEDIOL; CAPRYLHYDROXAMIC ACID; TRISODIUM ETHYLENEDIAMINE DISUCCINATE; POTASSIUM SORBATE; SODIUM BENZOATE

Advanced Eczema Relief Balm

Active ingredient

Colloidal Oatmeal 1%

Purpose

Skin protectant

Uses:

Temporarily protects and helps relieve minor skin irritation due to:

- eczema
- rashes

Warnings:

For external use only.

When using this product

- do not get into eyes.

Stop use and ask a doctor if

- condition worsens or symptoms last more than 7 days or clear up and occur again within a few days.

Keep out of reach of children

If swallowed, get medical help or contact a Poison Control Center immediately.

Directions:

Apply as needed. Safe to use every day on baby's sensitive skin.

Other information:

- Store at room temperature.

Inactive ingredients:

Water (Aqua), Carthamus Tinctorius (Safflower) Seed Oil, Olea Europaea (Olive) Fruit Oil, Beeswax, Coco-Caprylate/Caprate, Disteardimonium Hectorite, Propanediol, Bambusa Arundinacea Stem Extract, Polyglyceryl-3 Polyricinoleate, Polyglyceryl-3 Diisostearate, Magnesium Sulfate, Polyglyceryl-6 Polyricinoleate, Butyrospermum Parkii (Shea) Butter, Cocos Nucifera (Coconut) Oil, Pyrus Malus (Apple) Fruit Extract, Isosorbide Disunflowerseedate, Aloe Barbadensis Leaf Juice, Alpha-Glucan Oligosaccharide, Glycerin, Squalane, Allantoin, Tocopherol, 1,2-Hexanediol, Caprylhydroxamic Acid, Trisodium Ethylenediamine Disuccinate, Potassium Sorbate, Sodium Benzoate

Package/Label Principal Display Panel - Carton

H O N E S T®

soothe™

ADVANCED ECZEMA RELIEF BALM

FRAGRANCE FREE
Instant relief from dry, itchy skin

Prebiotics + colloidal oatmeal

Skin Protectant

NET WT 3.0 oz (85.0 g)

HOW TO USE ME: Made with care for flare-ups! Apply my steroid-free, hypoallergenic balm anytime for instant itch relief from dry, irritatated skin. Clinically tested to be safe for baby, I'm made with prebiotics to nourish the good bacteria, aka your skin's bodyguard.
Made in the USA with US and imported materials.

© 2023 Distributed by

The Honest Company, Inc., 12130 Millennium DR #500

Los Angeles, CA 90094

HONEST.COM•888-862-8818